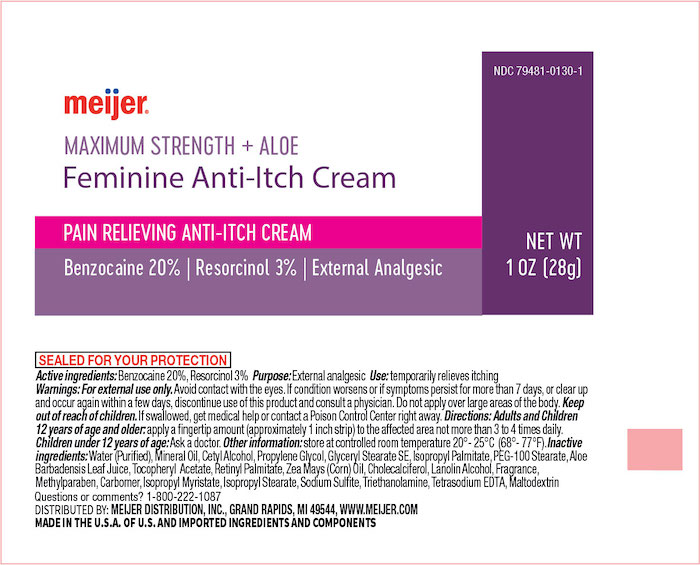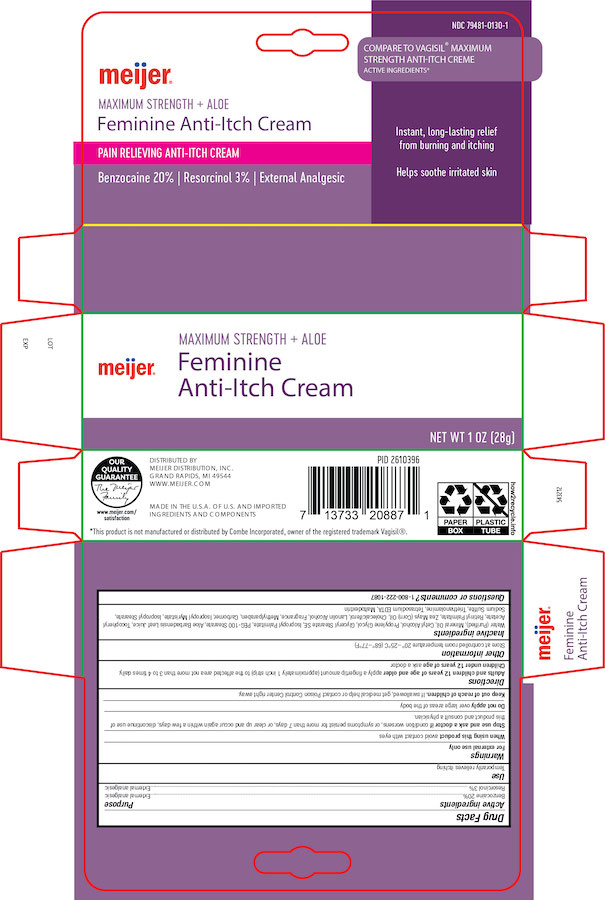 DRUG LABEL: Meijer Vagicaine
NDC: 79481-0130 | Form: CREAM
Manufacturer: Meijer, Inc.
Category: otc | Type: HUMAN OTC DRUG LABEL
Date: 20250130

ACTIVE INGREDIENTS: BENZOCAINE 200 mg/1 g; RESORCINOL 30 mg/1 g
INACTIVE INGREDIENTS: WATER; MINERAL OIL; CETYL ALCOHOL; PROPYLENE GLYCOL; GLYCERYL STEARATE SE; ISOPROPYL PALMITATE; PEG-100 STEARATE; ALOE VERA LEAF; .ALPHA.-TOCOPHEROL ACETATE; VITAMIN A PALMITATE; CORN OIL; CHOLECALCIFEROL; LANOLIN ALCOHOLS; METHYLPARABEN; CARBOMER HOMOPOLYMER TYPE B (ALLYL PENTAERYTHRITOL CROSSLINKED); ISOPROPYL MYRISTATE; ISOPROPYL STEARATE; SODIUM SULFITE; TROLAMINE; TETRASODIUM EDETATE DIHYDRATE; MALTODEXTRIN

Active Ingredient

Benzocaine 20%

Resorcinol 3%

Purpose

External analgesic

External analgesic

Uses

Temporarily Relieves Itching

Warnings

For external use only

Allergy Allert

Do not use this product if you have a history of allergy to local anesthetics such as procaine, butacaine, benzocaine or other –caine anesthetics.

Avoid contact with eyes

in case of contact rinse thoroughly and immediately with water.

Stop use and ask a doctor if

condition worsens, or if symptoms persist for more than 7 days, or clear up and occur again within a few days

Keep out of the reach of children

If swallowed, get medical help or contact a Poison Control Center right away.

Directions

Adults and children 12 years and older

Apply a finger tip amount (approxiamtely a 1 inch strip) to the affected areas not more than 3 to 4 times daily

Children under 12 years

ask a doctor

Other information

Questions?

Inactive ingredient

Water, Mineral Oil, Cetyl Alcohol, Propylene Glycol, Glyceryl Stearate, PEG-100 Stearate, Isopropyl Palmitate, Aloe Barbadensis Leaf Extract, Tocopheryl Acetate, Retinyl Palmitate, Zea Mays (Corn) Oil, Cholecalciferol, Lanolin Alcohol, Fragrance, Methylparaben, Carbomer, Isopropyl Myristate, Isopropyl Stearate, Sodium Sulfite, Triethanolamine, Trisodium EDTA, Maltodextrin

Principal Dispaly panel Tube and Carton

Equate NDC 79903-233-01

Maxium Strength Vagicaine + Aloe

Feminine Anti-itch Cream

Benzocaine 20%, Resorcinol 3%

External Analgesic

NET WT 1OZ (28g)